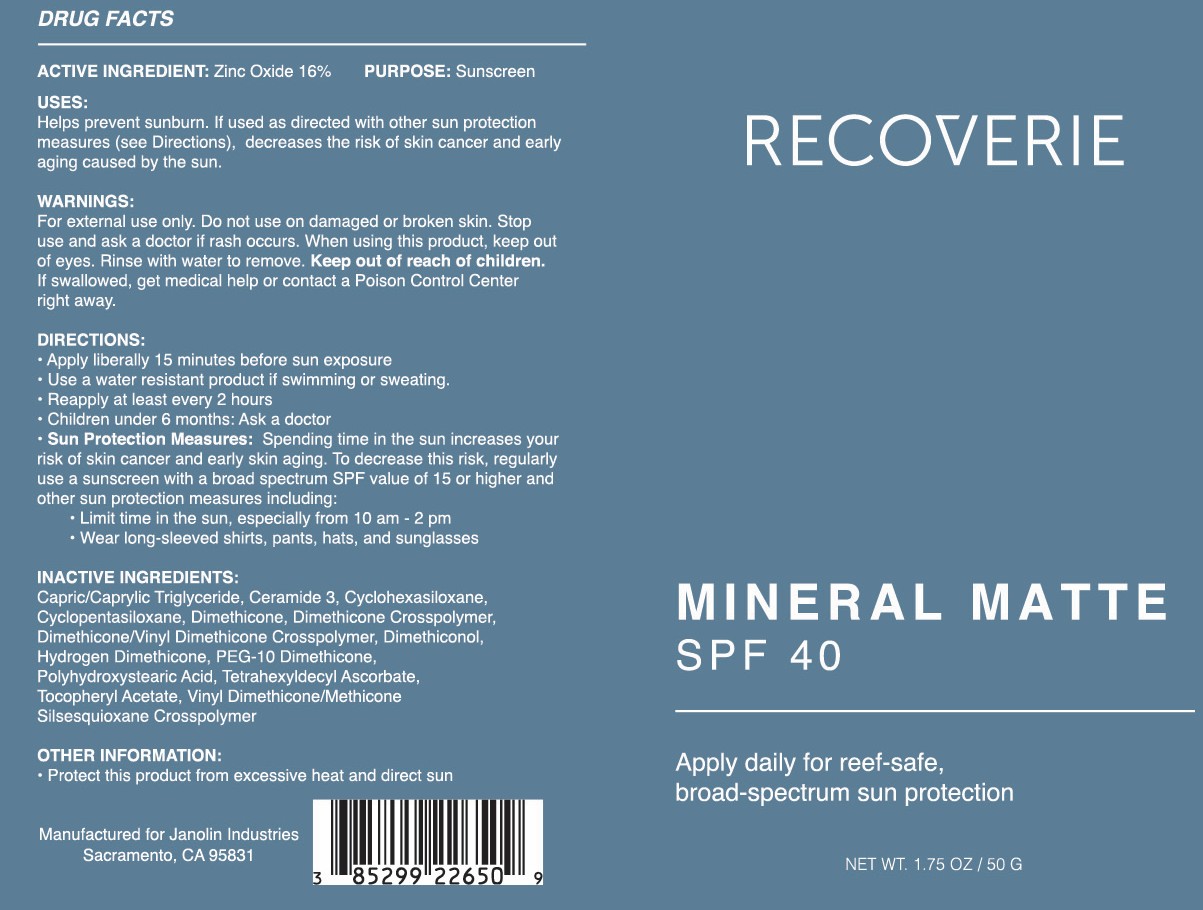 DRUG LABEL: Recoverie Mineral Matte
NDC: 85299-226 | Form: CREAM
Manufacturer: Clear Day Acne Clinic
Category: otc | Type: HUMAN OTC DRUG LABEL
Date: 20251210

ACTIVE INGREDIENTS: ZINC OXIDE 160 mg/1 g
INACTIVE INGREDIENTS: VINYL DIMETHICONE/METHICONE SILSESQUIOXANE CROSSPOLYMER; CAPRYLIC/CAPRIC TRIGLYCERIDE; DIMETHICONE/VINYL DIMETHICONE CROSSPOLYMER (SOFT PARTICLE); PEG-10 DIMETHICONE (600 CST); CYCLOHEXASILOXANE; ALPHA-TOCOPHEROL ACETATE; DIMETHICONOL (2000 CST); CYCLOPENTASILOXANE; HYDROGEN DIMETHICONE (20 CST); CERAMIDE 3; DIMETHICONE; POLYHYDROXYSTEARIC ACID (2300 MW); TETRAHEXYLDECYL ASCORBATE; DIMETHICONE CROSSPOLYMER

Active Ingredients:

Zinc Oxide 16%

Purpose:

Sunscreen

Uses:

Helps prevents sunburn. If used as directed with other sun protection measures (see Directions), decreases the risk of skin cancer and early skin aging caused by the sun.

Warnings:

For external use only. Do not use on damaged or broken skin. Stop use and ask a doctor if rash occurs. When using this product, keep out of eyes. Rinse with water to remove. Keep out of the reach of children. If swallowed, get medical help or contact a poison control center right away.

Directions:

• Apply liberally 15 minutes before sun exposure. • Reapply: • After 80 minutes of swimming or sweating • Immediately after towel drying • At least every 2 hours • Children under 6 months: Ask a doctor • Sun Protection Measures: Spending time in the sun increases your risk of skin cancer and early skin aging. To decrease this risk, regularly use a sunscreen with a Broad Spectrum SPF value of 15 or higher and other sun protection measures including: •Limit time in the sun, especially from 10 am-2 pm •Wear long-sleeved shirts, pants, hats, and sunglasses

Inactive Ingredients:

Capric/Caprylic Triglyceride, Ceramide 3, Cyclohexasiloxane, Cyclopentasiloxane, Dimethicone, Dimethicone Crosspolymer, Dimethicone/Vinyl Dimethicone Crosspolymer, Dimethiconol, Hydrogen Dimethicone, PEG-10 Dimethicone, Polyhydroxystearic Acid, Tetrahexyldecyl Ascorbate, Tocopheryl Acetate, Vinyl Dimethicone/Methicone Silsesquioxane Crosspolymer

Other Information:

Protect this product from excessive heat and direct sun

Warnings:

Keep out of reach of children